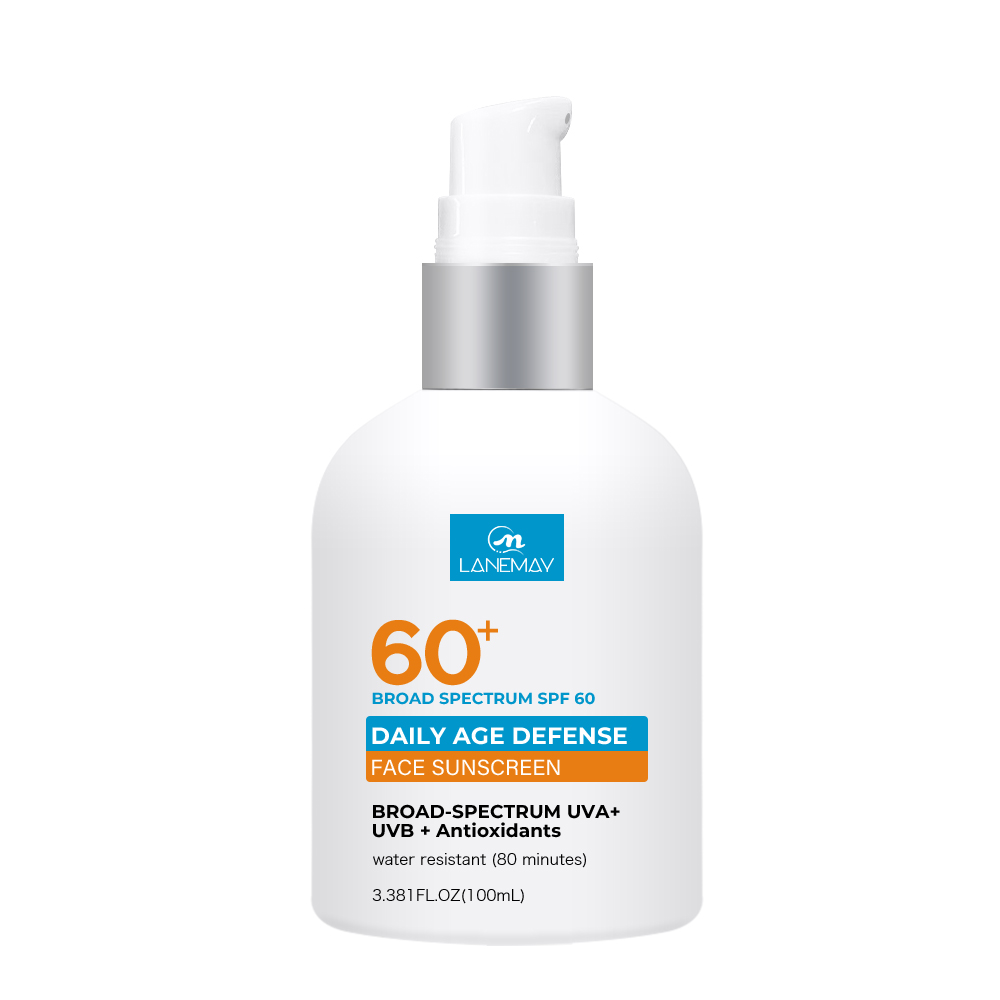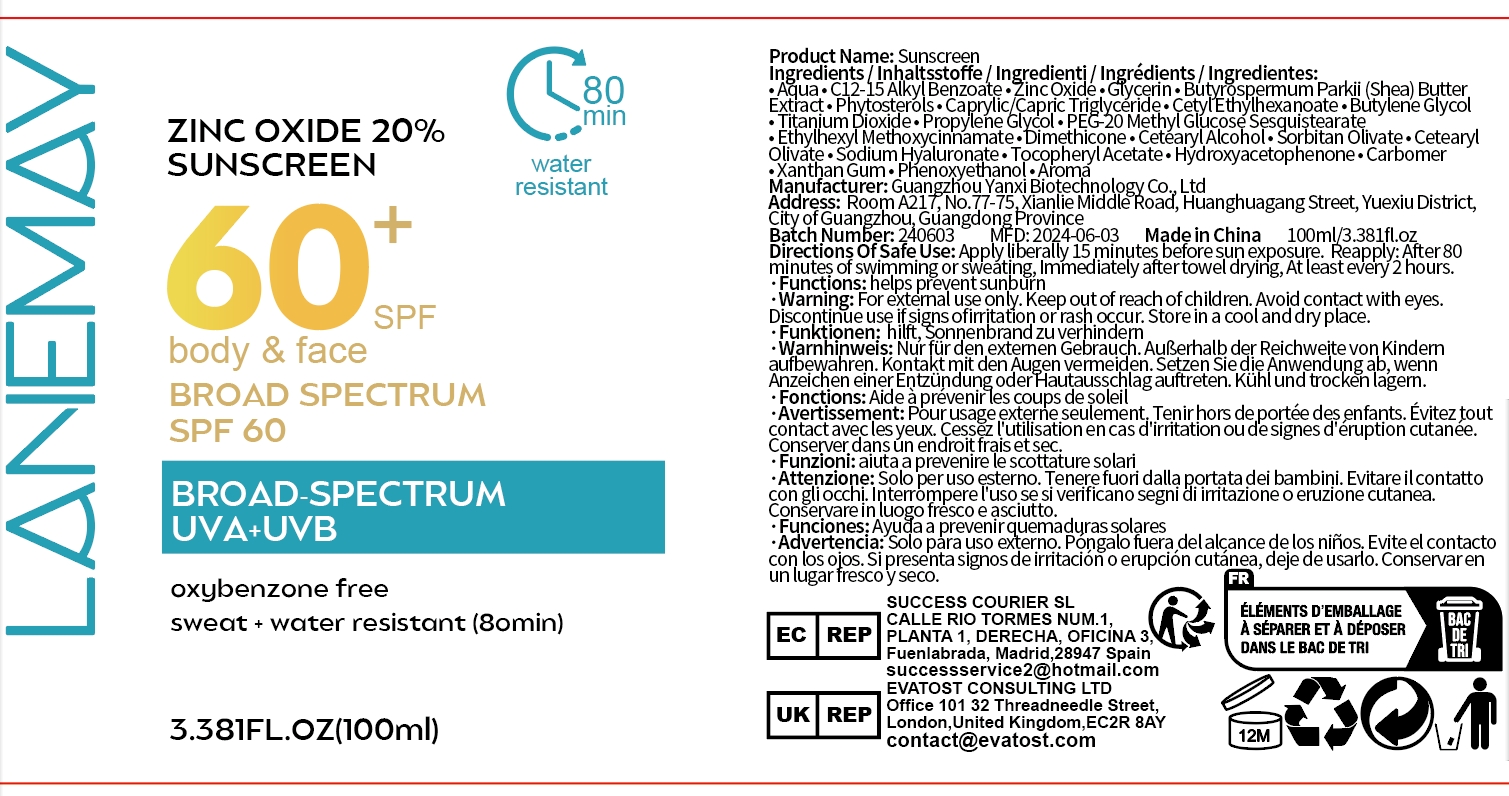 DRUG LABEL: Sunscreen
NDC: 84025-040 | Form: CREAM
Manufacturer: Guangzhou Yanxi Biotechnology Co., Ltd
Category: otc | Type: HUMAN OTC DRUG LABEL
Date: 20240603

ACTIVE INGREDIENTS: GLYCERIN 3 mg/100 mL; ZINC OXIDE 5 mg/100 mL
INACTIVE INGREDIENTS: WATER

DOSAGE AND ADMINISTRATION

Apply liberally 15 minutes before sun exposure. Reapply: After 80 minutes of swimming or sweating, Immediately after towel drying, At least every 2 hours.

INACTIVE INGREDIENT

aqua

INDICATIONS AND USAGE

Apply liberally 15 minutes before sun exposure. Reapply: After 80 minutes of swimming or sweating, Immediately after towel drying, At least every 2 hours.

WARNINGS

For external use only.

Keep out of reach of children.

PURPOSE

helps prevent sunbun